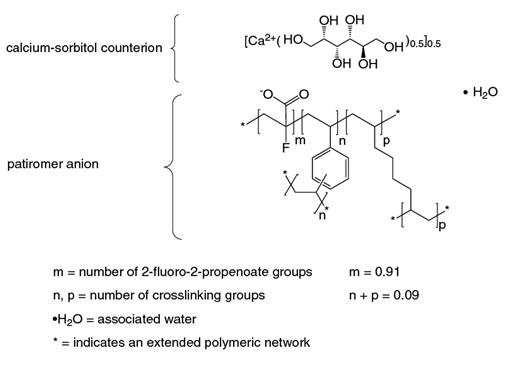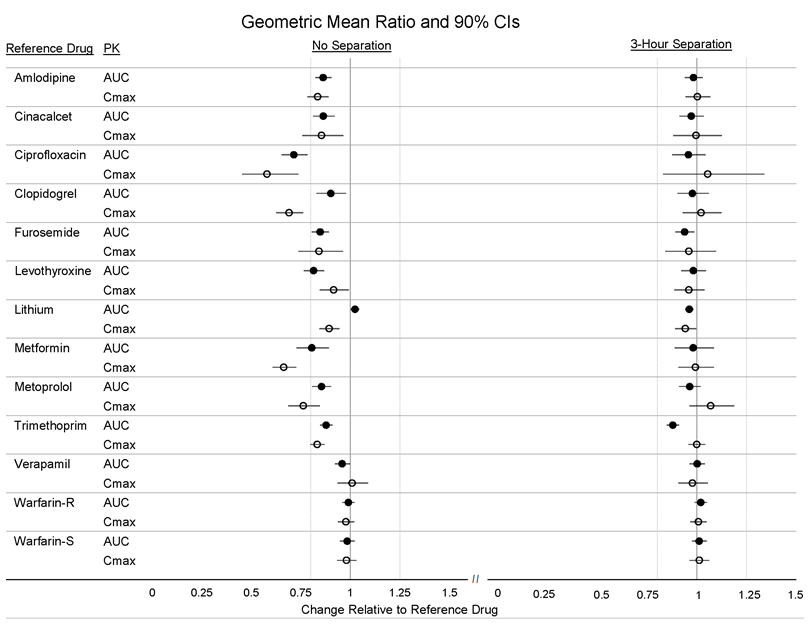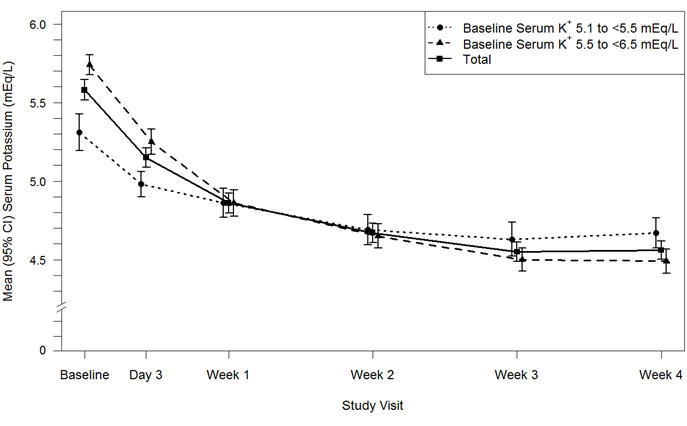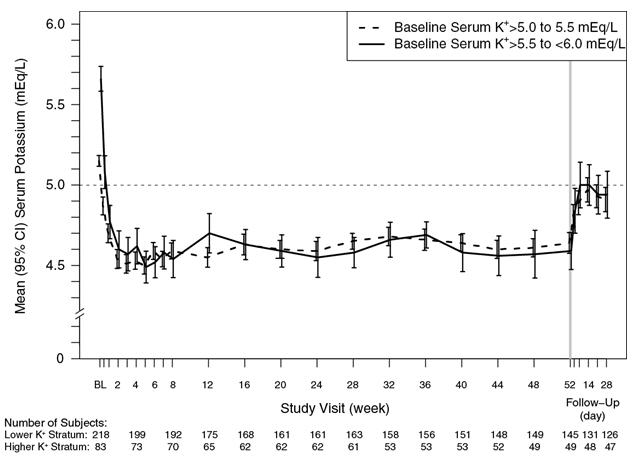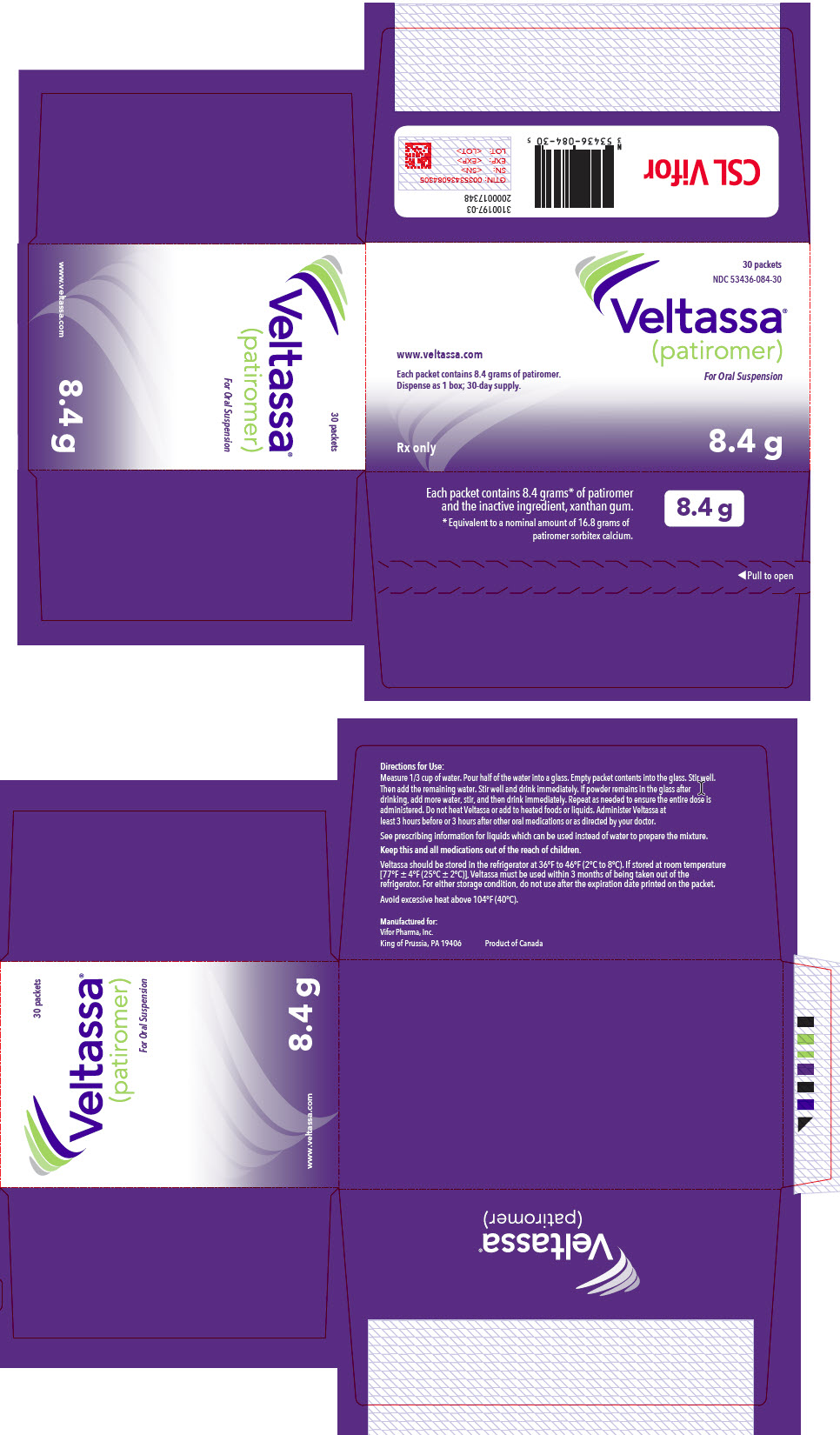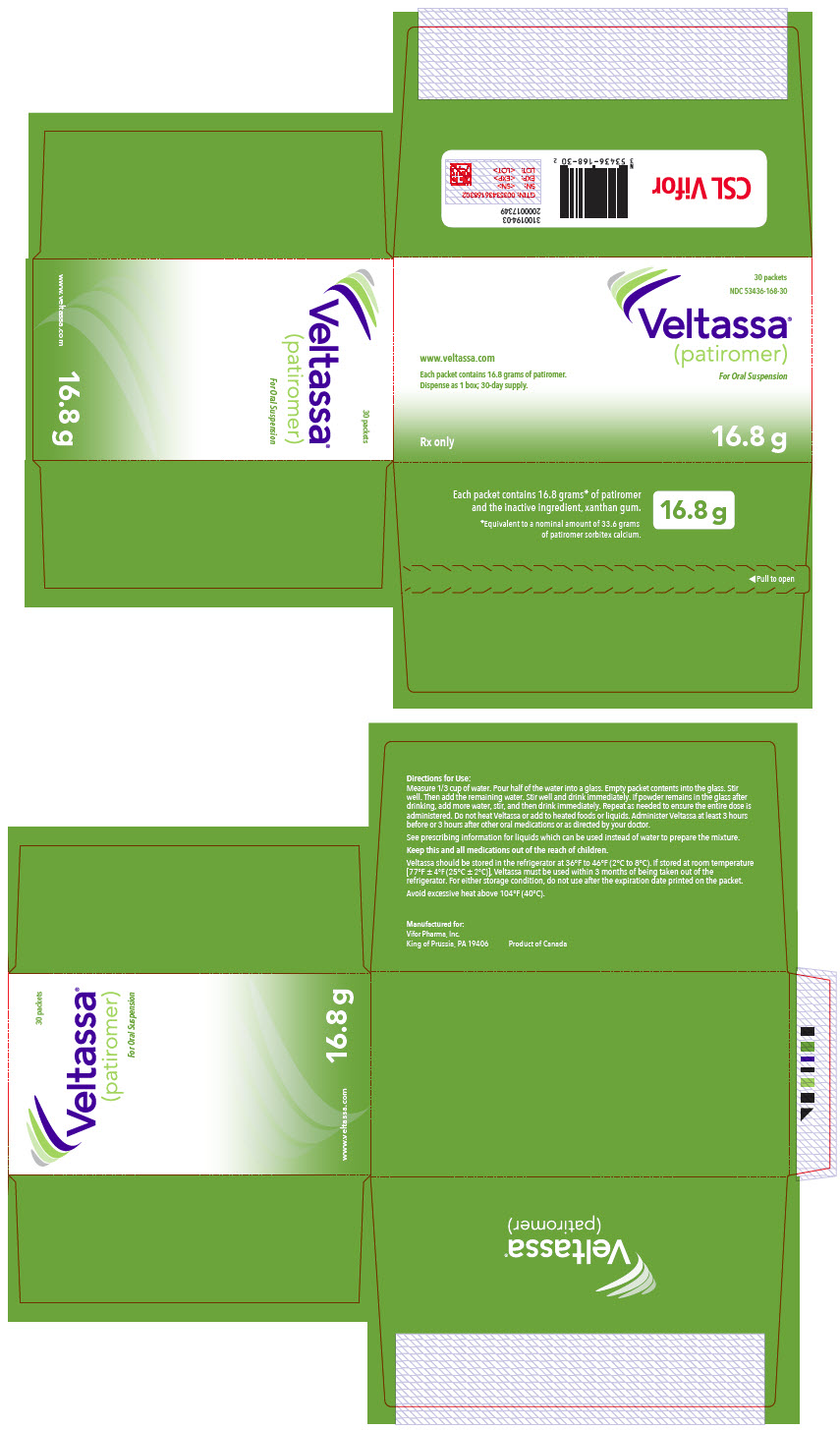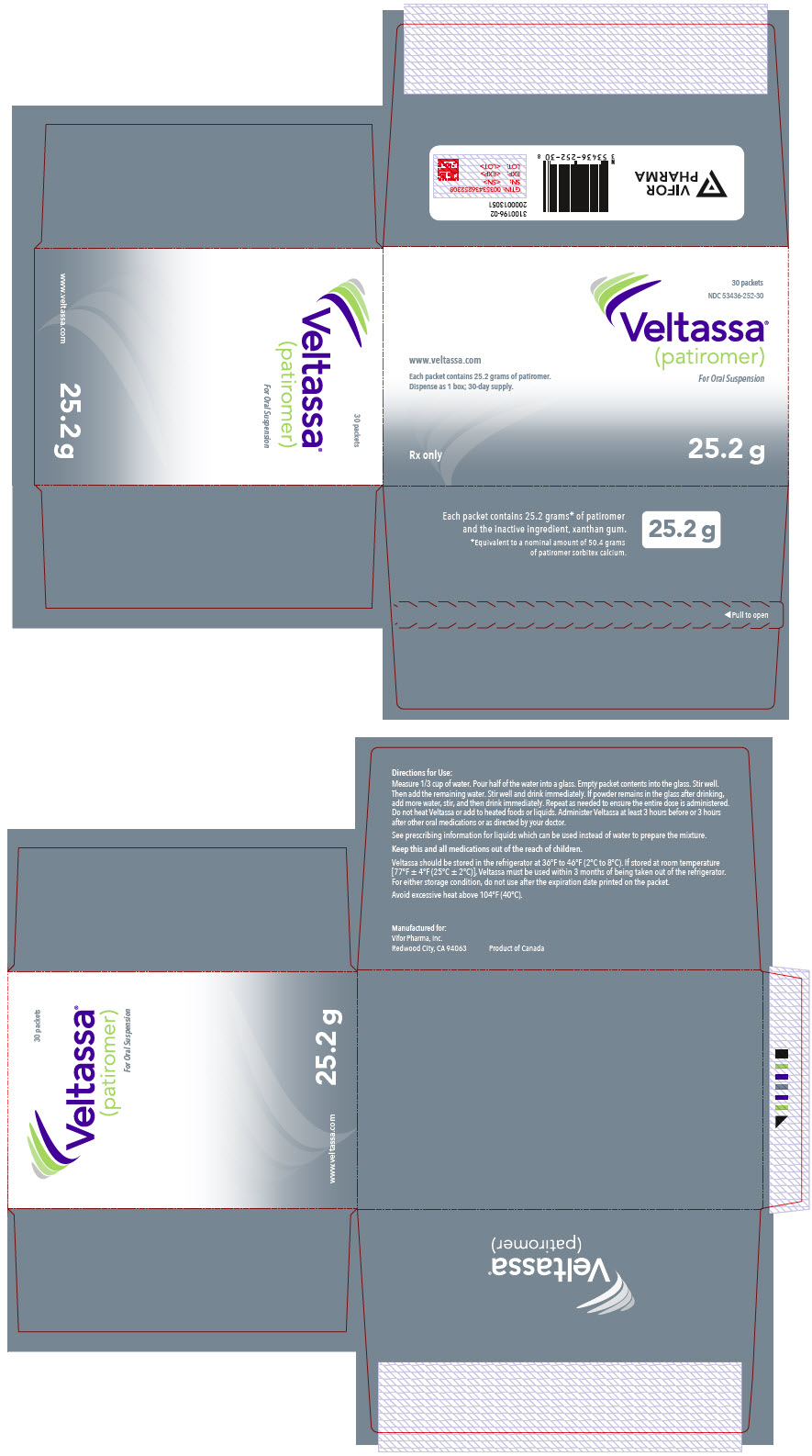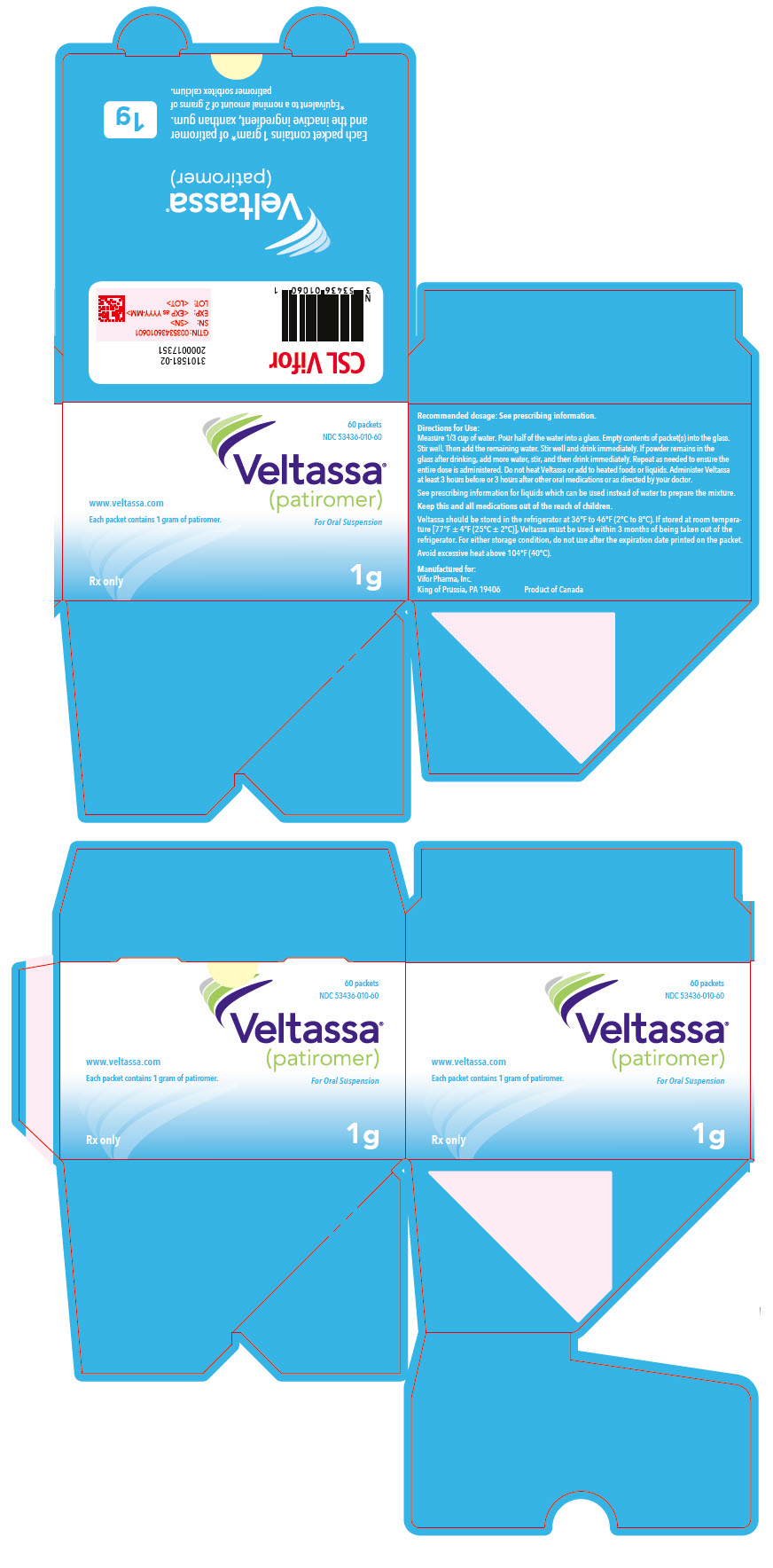 DRUG LABEL: VELTASSA
NDC: 53436-084 | Form: POWDER, FOR SUSPENSION
Manufacturer: Vifor Pharma, Inc.
Category: prescription | Type: HUMAN PRESCRIPTION DRUG LABEL
Date: 20250131

ACTIVE INGREDIENTS: patiromer 8.4 g/1 1
INACTIVE INGREDIENTS: xanthan gum 0.12 g/1 1

HIGHLIGHTS OF PRESCRIBING INFORMATION

These highlights do not include all the information needed to use VELTASSA® safely and effectively. See full prescribing information for VELTASSA.
VELTASSA (patiromer) for oral suspension
Initial U.S. Approval: 2015

1 INDICATIONS AND USAGE

Veltassa is a potassium binder indicated for the treatment of hyperkalemia in adults and pediatric patients ages 12 years and older. (1)

Limitation of Use

Veltassa should not be used as an emergency treatment for life-threatening hyperkalemia because of its delayed onset of action. (1)

2 DOSAGE AND ADMINISTRATION

- For adults, the recommended starting dose of Veltassa is 8.4 grams administered orally once daily. (2.2)
- For adults, adjust dose by 8.4 grams daily as needed at one-week intervals to obtain desired serum potassium target range. (2.2)
- For pediatric patients 12 to 17 years of age, the recommended starting dose of Veltassa is 4 grams administered orally once daily. (2.2)
- For pediatric patients 12 to 17 years of age, adjust dose by 4 grams daily as needed at one-week intervals to obtain desired serum potassium target range. (2.2)
- The maximum recommended dosage in adults and pediatric patients older than 12 years is 25.2 grams once daily. (2.2)

3 DOSAGE FORMS AND STRENGTHS

- Powder: 1 gram, 8.4 grams, 16.8 grams and 25.2 grams patiromer packets. (3)

4 CONTRAINDICATIONS

- Known hypersensitivity to Veltassa or any of its components. (4)

5 WARNINGS AND PRECAUTIONS

- Worsening of Gastrointestinal Motility. (5.1)
- Hypomagnesemia. (5.2)

6 ADVERSE REACTIONS

- Most common adverse reactions (incidence ≥ 2%) are constipation, hypomagnesemia, diarrhea, nausea, abdominal discomfort and flatulence. (6.1)

To report SUSPECTED ADVERSE REACTIONS, contact Vifor Pharma, Inc. at 1-844-VELTASSA (1-844-835-8277) or FDA at 1-800-FDA-1088 or www.fda.gov/medwatch.

7 DRUG INTERACTIONS

- Take other orally administered drugs at least 3 hours before or 3 hours after Veltassa except those shown to not have a clinically important interaction. (2.1, 7)

FULL PRESCRIBING INFORMATION

1 INDICATIONS AND USAGE

Veltassa is indicated for the treatment of hyperkalemia in adults and pediatric patients ages 12 years and older.

Limitation of Use: Veltassa should not be used as an emergency treatment for life-threatening hyperkalemia because of its delayed onset of action [see Clinical Pharmacology (12.2)].

2 DOSAGE AND ADMINISTRATION

2.1 General Information

Administer Veltassa at least 3 hours before or 3 hours after other oral medications except those shown to not have a clinically important interaction [see Drug Interactions (7) and Clinical Pharmacology (12.3)].

Do not heat Veltassa (e.g., microwave) or add to heated foods or liquids. Do not take Veltassa in its dry form.

2.2 Recommended Dosing and Titration

The recommended starting dose of Veltassa varies with age and is shown below. Multiple packets may be used to achieve the prescribed dose. Monitor serum potassium and adjust the dose of Veltassa based on the serum potassium level and the desired target range. The dose may be increased or decreased, as necessary, to reach the desired serum potassium concentration, up to a maximum dose of 25.2 grams once daily in adults and pediatric patients aged 12 years and older.

Adults: The recommended starting dose of Veltassa is 8.4 grams patiromer orally once daily. The dose can be up-titrated based on serum potassium level at 1-week or longer intervals, in increments of 8.4 grams.

Pediatric Patients Ages 12 years and older: The recommended starting dose of Veltassa is 4 grams patiromer orally once daily. The dose can be titrated based on serum potassium level at 1-week or longer intervals, in increments of 4 grams.

2.3 Preparation of Veltassa

Prepare each dose immediately prior to administration.

Measure 1/3 cup of water. Pour half of the water into a glass, then add the packet(s) of Veltassa and stir. Add the remaining half of the water and stir thoroughly. The powder will not dissolve and the mixture will look cloudy. Add more water to the mixture as needed for desired consistency.

Drink the mixture immediately. If powder remains in the glass after drinking, add more water, stir and drink immediately. Repeat as needed to ensure the entire dose is administered.

Other beverages or soft foods (e.g., apple sauce, yogurt, pudding) can be used instead of water to prepare the mixture by following the same steps as described above. A minimum volume of 45 mL (3 tablespoons) can be used to prepare doses up to and including 4 grams patiromer.

The potassium content of liquids or soft foods used to prepare the mixture should be considered as part of the dietary recommendations on potassium intake for each individual patient.

3 DOSAGE FORMS AND STRENGTHS

Veltassa is an off-white to light-brown powder for oral suspension packaged in single-use packets containing 1 gram, 8.4 grams, 16.8 grams or 25.2 grams patiromer.

4 CONTRAINDICATIONS

Veltassa is contraindicated in patients with a history of a hypersensitivity reaction to Veltassa or any of its components [see Adverse Reactions (6.1)].

5 WARNINGS AND PRECAUTIONS

5.1 Worsening of Gastrointestinal Motility

Avoid use of Veltassa in patients with severe constipation, bowel obstruction or impaction, including abnormal post-operative bowel motility disorders, because Veltassa may be ineffective and may worsen gastrointestinal conditions.

Patients with a history of bowel obstruction or major gastrointestinal surgery, severe gastrointestinal disorders, or swallowing disorders were not included in the clinical studies.

5.2 Hypomagnesemia

Veltassa binds to magnesium in the colon, which can lead to hypomagnesemia. In clinical studies, hypomagnesemia was reported as an adverse reaction in 5.3% of adult patients treated with Veltassa [see Adverse Reactions (6.1)]. Monitor serum magnesium. Consider magnesium supplementation in patients who develop low serum magnesium levels on Veltassa.

6 ADVERSE REACTIONS

The following adverse reaction is discussed in greater detail elsewhere in the label:

- Hypomagnesemia [see Warnings and Precautions (5.2)]

6.1 Clinical Trials Experience

Adult Patients

Because clinical trials are conducted under widely varying conditions, adverse reaction rates observed in the clinical trials of Veltassa cannot be directly compared to rates in the clinical trials of other drugs and may not reflect the rates observed in practice.

In the safety and efficacy clinical trials, 666 adult patients received at least one dose of Veltassa, including 219 exposed for at least 6 months and 149 exposed for at least one year.

Table 1 provides a summary of the most common adverse reactions (occurring in ≥ 2% of patients) in adult patients treated with Veltassa in these clinical trials. Most adverse reactions were mild to moderate. Constipation generally resolved during the course of treatment.

Table 1: Adverse Reactions Reported in ≥ 2% of Patients
Adverse Reactions | Adult Patients treated with Veltassa (N=666)
Constipation | 7.2%
Hypomagnesemia | 5.3%
Diarrhea | 4.8%
Nausea | 2.3%
Abdominal discomfort | 2.0%
Flatulence | 2.0%
Note: Diarrhea is an aggregate term for Diarrhea and frequent bowel movements. Abdominal discomfort is an aggregate term for Abdominal discomfort, abdominal pain, abdominal pain upper, and abdominal pain lower.

The most commonly reported adverse reactions leading to discontinuation of Veltassa were gastrointestinal adverse reactions (2.7%), including vomiting (0.8%), diarrhea (0.6%), constipation (0.5%) and flatulence (0.5%).

Mild to moderate hypersensitivity reactions were reported in 0.3% of adult patients treated with Veltassa in clinical trials. Reactions have included edema of the lips.

Laboratory Abnormalities

Approximately 4.7% of adult patients in clinical trials developed hypokalemia with a serum potassium value < 3.5 mEq/L.

Approximately 9% of adult patients in clinical trials developed hypomagnesemia with a serum magnesium value < 1.4 mg/dL.

Pediatric Patients

In a single-arm, open-label pediatric study, 14 patients 12 to 17 years of age received at least one dose of Veltassa, including 12 patients exposed for at least 25 weeks. The safety profile was generally similar to that observed in adult patients.

7 DRUG INTERACTIONS

Veltassa has the potential to bind some oral co-administered medications, which could decrease their gastrointestinal absorption. Binding of Veltassa to other oral medications not listed in Table 3 below could cause decreased gastrointestinal absorption and loss of efficacy when taken close to the time Veltassa is administered. Administer other oral medications at least 3 hours before or 3 hours after Veltassa [see Dosage and Administration (2.1) and Clinical Pharmacology (12.3)].

7.1 Clinically Important Interaction of Veltassa with Other Drugs

The in-vitro binding of the following drugs to patiromer was evaluated and potentially clinically significant binding was observed. Some drugs were subsequently tested in-vivo and significant reduction in systemic exposure was observed [see Dosage and Administration (2.1) and Clinical Pharmacology (12.3)].

Binding by Veltassa may reduce the systemic exposure and decrease the clinical efficacy of the co-administered drugs shown in Table 2. The administration of these drugs (and any drugs not listed in Table 3) should be separated by at least 3 hours from Veltassa.

Table 2: Clinically important drug interactions of Veltassa
Angiotensin II receptor blockers (ARB)
Telmisartan
β-adrenoceptor blockers (β-blocker)
Bisoprolol, carvedilol, nebivolol
Antibiotics
Ciprofloxacin
Anti-Parathyroid Agents and Thyroid Preparations
Levothyroxine
Blood Glucose Lowering Drugs
Metformin
Immunosuppressants
Mycophenolate mofetil
Others
Quinidine, thiamine

7.2 No Observed Clinically Important Interaction of Veltassa with Other Drugs

The binding of the following drugs to patiromer was evaluated [see Clinical Pharmacology (12.3)] and no clinically significant binding was observed. No separation of dosing is required for these drugs.

Table 3: No observed clinically important drug interactions of Veltassa

Angiotensin-converting enzyme (ACE) inhibitors
Benazepril, captopril, enalapril, fosinopril, lisinopril, perindopril, quinapril, ramipril, trandolapril

Angiotensin II receptor blockers (ARB)
Azilsartan, candesartan, irbesartan, losartan, olmesartan, valsartan

β-adrenoceptor blockers (β-blocker)
Metoprolol

Loop diuretics
Furosemide, bumetanide, torasemide

Mineralocorticoid receptor antagonists (MRA)
Eplerenone, finerenone, spironolactone

Neprilysin inhibitors
Sacubitril

Sodium-glucose cotransporter-2 (SGLT-2) inhibitors
Canagliflozin, dapagliflozin, empagliflozin

Antibiotics
Trimethoprim, amoxicillin, cephalexin

Anticoagulants
Warfarin, apixaban, rivaroxaban

Anti-parathyroid agents and Thyroid preparations
Cinacalcet

Antithrombotic agents
Clopidogrel, acetylsalicylic acid

Blood glucose lowering drugs
Glipizide

Calcium channel blockers
Amlodipine, verapamil

Immunosuppressants
Tacrolimus

Others
Lithium, allopurinol, atorvastatin, digoxin, phenytoin, riboflavin, sevelamer

8 USE IN SPECIFIC POPULATIONS

8.1 Pregnancy

Risk Summary

Veltassa is not absorbed systemically following oral administration and maternal use is not expected to result in fetal risk.

8.2 Lactation

Risk Summary

Veltassa is not absorbed systemically by the mother, so breastfeeding is not expected to result in risk to the infant.

8.4 Pediatric Use

The safety and effectiveness of Veltassa for lowering serum potassium levels have been established in pediatric patients ages 12 years and older. Use of Veltassa for this indication is supported by evidence from an adequate and well-controlled study in adults, with additional pharmacodynamic and safety data in pediatric patients aged 12 years and older [see Dosage and Administration (2.2), Adverse Reactions (6.1), and Clinical Studies (14.3)].

Safety and efficacy have not been established in pediatric patients below the age of 12 years. Although the pediatric study included 9 patients 6 to less than 12 years of age, the dosing regimen that was evaluated in these patients did not appear to be effective in reducing serum potassium levels in this age group after 2 weeks. The starting dose of Veltassa in this age group was 2 g/day and the median dose at Day 14 was 6 g/day. In this age group the mean change in serum potassium from Baseline to Day 14 was -0.1 mEq/L (95% CI -0.7, 0.4). Because the available data are not sufficient to determine a safe and effective dosing regimen in patients 6 to less than 12 years of age, labeling recommendations cannot be provided for this age group.

8.5 Geriatric Use

Of the 666 patients treated with Veltassa in clinical studies, 60% were age 65 and over, and 20% were age 75 and over. No overall differences in effectiveness were observed between these patients and younger patients. Patients age 65 and older reported more gastrointestinal adverse reactions than younger patients.

8.6 Renal Impairment

Of the 666 adult patients treated with Veltassa in clinical studies, 93% had chronic kidney disease (CKD). All 14 pediatric patients ages 12 years and older treated with Veltassa in the clinical study had chronic kidney disease. No special dosing adjustments are needed for patients with renal impairment.

10 OVERDOSAGE

Doses of Veltassa in excess of 50.4 grams per day have not been tested. Excessive doses of Veltassa may result in hypokalemia. Restore serum potassium if hypokalemia occurs.

11 DESCRIPTION

Veltassa is a powder for suspension in water for oral administration. The active ingredient is patiromer sorbitex calcium which consists of the active moiety, patiromer, a non-absorbed potassium-binding polymer, and a calcium-sorbitol counterion. Each gram of patiromer is equivalent to a nominal amount of 2 grams of patiromer sorbitex calcium.

The chemical name for patiromer sorbitex calcium is cross-linked polymer of calcium 2-fluoroprop-2-enoate with diethenylbenzene and octa-1,7-diene, combination with D-glucitol.

Patiromer sorbitex calcium is an amorphous, free-flowing powder that is composed of individual spherical beads. Patiromer sorbitex calcium is insoluble in solvents such as water, 0.1 M HCl, n-heptane and methanol. The chemical structure of patiromer sorbitex calcium is presented in Figure 1.

Figure 1: Chemical Structure of Patiromer Sorbitex Calcium

Each packet of Veltassa contains 1 gram, 8.4 grams, 16.8 grams or 25.2 grams of patiromer, the active moiety. The inactive ingredient is xanthan gum.

12 CLINICAL PHARMACOLOGY

12.1 Mechanism of Action

Veltassa is a non-absorbed, cation exchange polymer that contains a calcium-sorbitol counterion.

Veltassa increases fecal potassium excretion through binding of potassium in the lumen of the gastrointestinal tract. Binding of potassium reduces the concentration of free potassium in the gastrointestinal lumen, resulting in a reduction of serum potassium levels.

12.2 Pharmacodynamics

In a Phase 1 study in healthy adult subjects (6 to 8 subjects per group), Veltassa (0 grams to 50.4 grams per day) administered three times a day for 8 days caused a dose-dependent increase in fecal potassium excretion. A corresponding dose-dependent decrease in urinary potassium excretion with no change in serum potassium were also observed. Compared to placebo, Veltassa doses of 25.2 and 50.4 grams per day significantly decreased mean daily urinary potassium excretion.

In a Phase 1, open-label, multiple-dose crossover study in 12 healthy subjects, 25.2 grams of patiromer per day was administered orally as a once daily, twice daily or thrice daily regimen for 6 days in a randomly assigned order. A significant increase in mean daily fecal potassium excretion and concomitant decrease in mean daily urinary potassium excretion were observed during the treatment periods for all three dosing regimens. The mean increase in fecal potassium excretion ranged from 1283 to 1550 mg/day, and the mean decrease in urinary potassium excretion ranged from 1438 to 1534 mg/day across the three dosing regimens. No significant differences were observed among the dosing regimens with respect to mean daily fecal potassium and urinary potassium excretion. This was true for the overall comparison among the three dosing regimens, as well as for the pairwise comparisons.

In an open-label, uncontrolled study, 25 patients with hyperkalemia (mean baseline serum potassium of 5.9 mEq/L) and chronic kidney disease were given a controlled potassium diet for 3 days, followed by 16.8 grams patiromer daily (as divided doses) for 2 days while the controlled diet was continued. A statistically significant reduction in serum potassium (-0.2 mEq/L) was observed at 7 hours after the first dose. Serum potassium levels continued to decline during the 48-hour treatment period (-0.8 mEq/L at 48 hours after the first dose). Potassium levels remained stable for 24 hours after the last dose, then rose during the 4-day observation period following discontinuation of Veltassa.

12.3 Pharmacokinetics

Absorption

In radiolabeled ADME studies in rats and dogs, patiromer was not systemically absorbed and was excreted in the feces. Quantitative whole-body autoradiography analysis in rats demonstrated that radioactivity was limited to the gastrointestinal tract, with no detectable level of radioactivity in any other tissues or organs.

Effect of Food

Veltassa can be taken with or without food. In an open-label study, 114 patients with hyperkalemia were randomized to Veltassa once daily with food or without food. Serum potassium at the end of treatment, the change from baseline in serum potassium, and the mean dose of Veltassa were similar between groups.

Drug Interactions

Veltassa has the potential to bind some oral co-administered medications, which could decrease their gastrointestinal absorption.

Fifty-six (56) drugs were tested in-vitro to determine the potential for interaction with Veltassa [see Drug Interactions (7)]. For oral drug products not listed in Table 3, administration of patiromer should be separated by at least 3 hours as a precautionary measure.

Twelve (12) drugs that showed an in vitro interaction were subsequently tested in vivo. These studies in healthy volunteers showed that Veltassa did not alter the systemic exposure of amlodipine, cinacalcet, clopidogrel, furosemide, lithium, metoprolol, trimethoprim, verapamil or warfarin when coadministered with Veltassa. Veltassa decreased the systemic exposure of coadministered ciprofloxacin, levothyroxine and metformin. However, there was no interaction when Veltassa and these drugs were taken 3 hours apart (Figure 2) [see Drug Interactions (7)].

Figure 2: Effects of Veltassa on the Pharmacokinetic Exposures of Other Orally Administered Medications with No Dosing Separation and with a 3-Hour Separation

13 NONCLINICAL TOXICOLOGY

13.1 Carcinogenesis, Mutagenesis, Impairment of Fertility

Patiromer was not genotoxic in the reverse mutation test (Ames assay), chromosome aberration or rat micronucleus assays.

Carcinogenicity studies have not been performed.

Patiromer did not impair the fertility in male or female rats at doses up to 10-fold the maximum recommended human dose (MRHD).

14 CLINICAL STUDIES

14.1 Two-Part, Randomized Withdrawal Study

The efficacy of Veltassa was demonstrated in a two-part, single-blind randomized withdrawal study that evaluated Veltassa in hyperkalemic patients with CKD on stable doses of at least one renin-angiotensin-aldosterone system inhibitor (i.e., angiotensin-converting enzyme inhibitor, angiotensin II receptor blocker, or aldosterone antagonist).

In Part A, 243 patients were treated with Veltassa for 4 weeks. Patients with a baseline serum potassium of 5.1 mEq/L to < 5.5 mEq/L received a starting Veltassa dose of 8.4 grams patiromer per day (as a divided dose) and patients with a baseline serum potassium of 5.5 mEq/L to < 6.5 mEq/L received a starting Veltassa dose of 16.8 grams patiromer per day (as a divided dose). The dose of Veltassa was titrated, as needed, based on the serum potassium level, assessed starting on Day 3 and then at weekly visits (Weeks 1, 2 and 3) to the end of the 4-week treatment period, with the aim of maintaining serum potassium in the target range (3.8 mEq/L to < 5.1 mEq/L).

The mean age of patients was 64 years, 58% of patients were men, and 98% were white. Approximately 97% of patients had hypertension, 57% had type 2 diabetes, and 42% had heart failure.

Results for the Part A primary endpoint, the change in serum potassium from Baseline to Week 4, are summarized in Table 4. Mean serum potassium over time for the intent-to-treat population is displayed in Figure 3. For the Part A secondary endpoint, 76% (95% CI: 70%, 81%) of patients had a serum potassium in the target range of 3.8 mEq/L to < 5.1 mEq/L at Week 4. The mean daily doses of Veltassa were 13 grams and 21 grams in patients with serum potassium of 5.1 to < 5.5 mEq/L and 5.5 to < 6.5 mEq/L, respectively.

Table 4: Veltassa Treatment Phase (Part A): Primary Endpoint
 |  | Baseline, mean (SD) | Week 4 Change from Baseline, Mean ± SE (95% CI) | p-value
Baseline Potassium 5.1 to <5.5 mEq/L (n=90) | Serum Potassium (mEq/L) | 5.31 (0.57) | -0.65 ± 0.05 (-0.74, -0.55)
Baseline Potassium 5.5 to <6.5 mEq/L (n=147) | Serum Potassium (mEq/L) | 5.74 (0.40) | -1.23 ± 0.04 (-1.31, -1.16)
Overall Population (n=237) | Serum Potassium (mEq/L) | 5.58 (0.51) | -1.01 ± 0.03 (-1.07, -0.95) | < 0.001

Figure 3: Estimated Mean (95% CI) of Central Serum Potassium (mEq/L) Over Time

In Part B, 107 patients with a Part A baseline serum potassium of 5.5 mEq/L to < 6.5 mEq/L and whose serum potassium was in the target range (3.8 mEq/L to < 5.1 mEq/L) at Part A Week 4 and still receiving RAAS inhibitor medication were randomized to continue Veltassa or to receive placebo to evaluate the effect of withdrawing Veltassa on serum potassium. In patients randomized to Veltassa, the mean daily dose was 21 grams at the start of Part B and during Part B.

The Part B primary endpoint was the change in serum potassium from Part B baseline to the earliest visit at which the patient's serum potassium was first outside of the range of 3.8 to < 5.5 mEq/L, or to Part B Week 4 if the patient's serum potassium remained in the range. In Part B, serum potassium rose by 0.72 mEq/L in patients who were switched to placebo, versus no change in patients who remained on Veltassa. Results are summarized in Table 5.

Table 5: Randomized, Placebo-Controlled Withdrawal Phase (Part B): Primary Endpoint
 | Placebo (n=52) | Veltassa (n=55) | Difference
 | Placebo (n=52) | Veltassa (n=55) | Estimate (95% CI) | p-value
Estimated Median Change in Serum Potassium from Baseline (mEq/L) | 0.72 | 0.00 | 0.72 (0.46, 0.99) | < 0.001

More placebo patients (91%; 95% CI: 83%, 99%) developed a serum potassium ≥ 5.1 mEq/L at any time during Part B than Veltassa patients (43%; 95% CI: 30%, 56%), p < 0.001. More placebo patients (60%; 95% CI: 47%, 74%) developed a serum potassium ≥ 5.5 mEq/L at any time during Part B than Veltassa patients (15%; 95% CI: 6%, 24%), p < 0.001.

14.2 One-Year Study

The effect of treatment with Veltassa for up to 52 weeks was evaluated in an open-label study of 304 hyperkalemic patients with CKD and type 2 diabetes mellitus on RAAS inhibitor therapy. Figure 4 shows that the treatment effect on serum potassium was maintained during continued therapy. In patients with a baseline serum potassium of > 5.0 to 5.5 mEq/L who received an initial dose of 8.4 grams patiromer per day (as a divided dose), the mean daily dose was 14 grams; in those with a baseline serum potassium of > 5.5 to < 6.0 mEq/L who received an initial dose of 16.8 grams patiromer per day (as a divided dose), the mean daily dose was 20 grams during the entire study.

Figure 4: Mean (95% CI) Serum Potassium over Time

14.3 Pediatric Study

The potassium-lowering effect of Veltassa was evaluated in an open-label, single-arm study in pediatric patients 12 to 17 years of age with CKD and hyperkalemia. The study included an initial 14-day dose finding phase, followed by an up to 24-week long-term (LT) treatment phase and a 2-week follow-up period. Veltassa was given once daily as a powder for oral suspension. The dose of Veltassa was titrated, as needed, based on the serum potassium level, assessed starting on Day 3 and then at Day 7 and Day 14, with the aim of maintaining serum potassium in the target range (3.8 mEq/L to < 5.0 mEq/L).

All 14 patients 12 to 17 years of age completed the dose finding phase. The mean age was 14.5 years, 79% were male, and all were white. The average weight at baseline was 51 kg and 57% of patients had a baseline eGFR <30 mL/min/1.73 m^2. Approximately 57% were on RAAS inhibitor therapy at baseline. The mean (SD) baseline serum potassium was 5.5 mEq/L (0.3 mEq/L).

The mean change in serum potassium from baseline to Day 14 was -0.5 mEq/L (95% CI -0.8, -0.2). The proportion of patients 12 to 17 years of age with a serum potassium within the normal range was 50% at Day 14. The median dose at Day 14 was 4.2 g/day.

16 HOW SUPPLIED/STORAGE AND HANDLING

16.1 How Supplied

Veltassa is supplied as a powder for oral suspension formulated with xanthan gum. Veltassa is packaged in single-use packets containing 1 gram, 8.4 grams, 16.8 grams or 25.2 grams patiromer as follows:

Veltassa (grams) | Carton of 4 Packets | Carton of 30 Packets | Carton of 60 Packets
1 | - | - | NDC 53436-010-60
8.4 | NDC 53436-084-04 | NDC 53436-084-30 | -
16.8 | - | NDC 53436-168-30 | -
25.2 | - | NDC 53436-252-30 | -

16.2 Stability and Storage

Veltassa should be stored in the refrigerator at 2°C to 8°C (36°F to 46°F).

If stored at room temperature (25°C ± 2°C [77°F ± 4°F]), Veltassa must be used within 3 months of being taken out of the refrigerator. For either storage condition, do not use Veltassa after the expiration date printed on the packet.

Avoid exposure to excessive heat above 40°C (104°F).

17 PATIENT COUNSELING INFORMATION

Drug Interactions

Advise patients who are taking other oral medication that separation of dosing of Veltassa by at least 3 hours (before or after) may be needed except those shown to not have a clinically important interaction in Table 3 above [see Drug Interactions (7)].

Dosing Recommendations

Inform patients to take Veltassa as directed and adhere to their prescribed diets.

Inform patients that Veltassa should not be heated (e.g., microwaved) or added to heated foods or liquids and should not be taken in its dry form.

Manufactured for:

Vifor Pharma, Inc.
King of Prussia, PA 19406

Version 11; January 2025

PRINCIPAL DISPLAY PANEL - 8.4 g Packet Carton

30 packets
NDC 53436-084-30

Veltassa®
(patiromer)

For Oral Suspension

www.veltassa.com

Each packet contains 8.4 grams of patiromer.
Dispense as 1 box; 30-day supply.

Rx only

8.4 g

PRINCIPAL DISPLAY PANEL - 16.8 g Packet Carton

30 packets
NDC 53436-168-30

Veltassa®
(patiromer)

For Oral Suspension

www.veltassa.com

Each packet contains 16.8 grams of patiromer.
Dispense as 1 box; 30-day supply.

Rx only

16.8 g

PRINCIPAL DISPLAY PANEL - 25.2 g Packet Carton

30 packets
NDC 53436-252-30

Veltassa®
(patiromer)

For Oral Suspension

www.veltassa.com

Each packet contains 25.2 grams of patiromer.
Dispense as 1 box; 30-day supply.

Rx only

25.2 g

PRINCIPAL DISPLAY PANEL - 1 g Packet Carton

60 packets
NDC 53436-010-60

Veltassa®
(patiromer)

For Oral Suspension

www.veltassa.com

Each packet contains 1 gram of patiromer.

Rx only

1 g